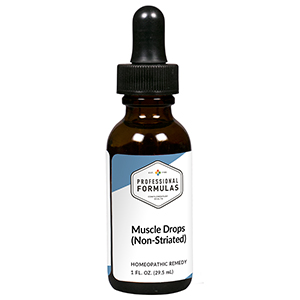 DRUG LABEL: Muscle Drops (Non-Striated)
NDC: 63083-9629 | Form: LIQUID
Manufacturer: Professional Complementary Health Formulas
Category: homeopathic | Type: HUMAN OTC DRUG LABEL
Date: 20190815

ACTIVE INGREDIENTS: BOS TAURUS LIGAMENT 12 [hp_X]/29.5 mL
INACTIVE INGREDIENTS: ALCOHOL; WATER

RMSN

ACTIVE INGREDIENTS

Muscle (non-striated) 12X

QUESTIONS

Professional Formulas

PO Box 2034 Lake Oswego, OR 97035

INDICATIONS

For the temporary relief of inflammation, urinary discomfort or difficulity, mild abdominal pain, constipation or diarrhea, shortness of breath, dizziness, or fatigue.*

PURPOSE

*Claims based on traditional homeopathic practice, not accepted medical evidence. Not FDA evaluated.

WARNINGS

Severe or persistent symptoms may be serious. Consult a doctor promptly. Keep out of the reach of children. In case of overdose, get medical help or contact a poison control center right away. If pregnant or breastfeeding, ask a healthcare professional before use.

Keep out of the reach of children.

PREGNANCY OR BREAST FEEDING

If pregnant or breastfeeding, ask a healthcare professional before use.

DIRECTIONS

Place drops under tongue 30 minutes before/after meals. Adults and children 12 years and over: Take 10 drops up to 3 times per day. Consult a physician for use in children under 12 years of age.

OTHER INFORMATION

Tamper resistant. If seal is broken, do not use. After opening, close container tightly and store at room temperature away from heat.

INACTIVE INGREDIENTS

20% ethanol, purified water.

LABEL

Est 1985

Professional Formulas

Complementary Health

Muscle Drops (Non-Striated)

Homeopathic Remedy

1 FL. OZ. (29.5 mL)